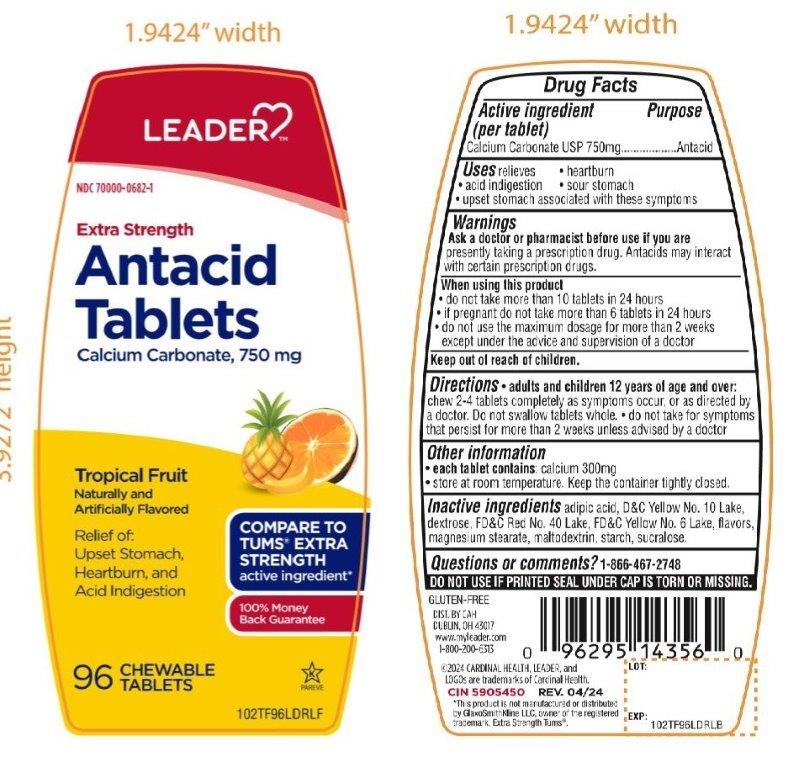 DRUG LABEL: ANTACID

NDC: 70000-0682 | Form: TABLET, CHEWABLE
Manufacturer: CARDINAL HEALTH 110, LLC.
Category: otc | Type: HUMAN OTC DRUG LABEL
Date: 20251014

ACTIVE INGREDIENTS: CALCIUM CARBONATE 750 mg/1 1
INACTIVE INGREDIENTS: DEXTROSE, UNSPECIFIED FORM; ADIPIC ACID; MAGNESIUM STEARATE; MALTODEXTRIN; FD&C RED NO. 40; STARCH, CORN; SUCRALOSE; FD&C YELLOW NO. 6; D&C YELLOW NO. 10

Cardinal Health Extra Strength Antacid Tablets Drug Facts

Active ingredient (in each tablet)

Calcium carbonate USP 750mg

Purpose

Antacid

Uses

relieves

- heartburn
- sour stomach
- acid indigestion
- upset stomach associated with these symptoms

Warnings

Ask a doctor or pharmacist before use if you are

taking a prescription drug. Antacids may interact with certain prescription drugs.

When using this product

- do not take more than 10 tablets in 24 hours
- If pregnant do not take more than 6 tablets in 24 hours
- do not use the maximum dosage for more than 2 weeks except under the advice and supervision of a doctor

Directions

- Adults and children 12 years of age and over:Chew 2 - 4 tablets completely as symptoms occur, or as directed by a doctor
- Do not swallow tablets whole. Do not take for symptoms that persist for more than 2 weeks unless advised by a doctor.

Other information

- Each tablet contains: calcium 300mg
- Store a room temperature
- Keep this container tightly closed

Safety sealed: Do not use if printed seal under cap is torn or missing.

Inactive ingredients

adipic acid, D&C Yellow 10 Lake, dextrose, FD&C Red No.40 Lake, FD&C Yellow No 6 Lake, flavors, magnesium stearate, maltodextrin, , starch, sucralose,

Questions?

1-866-467-2748

Principal Display Panel

LEADER™

NDC# 70000-0682-1

COMPARE TO TUMS® EXTRA STRENGTH active ingredient*

Extra Strength

Antacid Tablets

Calcium Carbonate 750 mg

Tropical Fruit

Naturally and Artificially Flavored

Relief of:

Upset Stomach,

Heartburn, and

Acid Indigestion

100% Money Back Guarantee

96 CHEWABLE TABLETS

Distributed By: CAH

Dublin, Ohio 43017

www.myleader.com

1-800-200-6313

©2024 CARDINAL HEALTH, LEADER, and LOGOs are trademarks of Cardinal Health.

CIN 5905450

REV. 04/24

*This product is not manufactured or distributed by GlaxoSmithKline, owner of the registered trademark Extra Strength Tums®